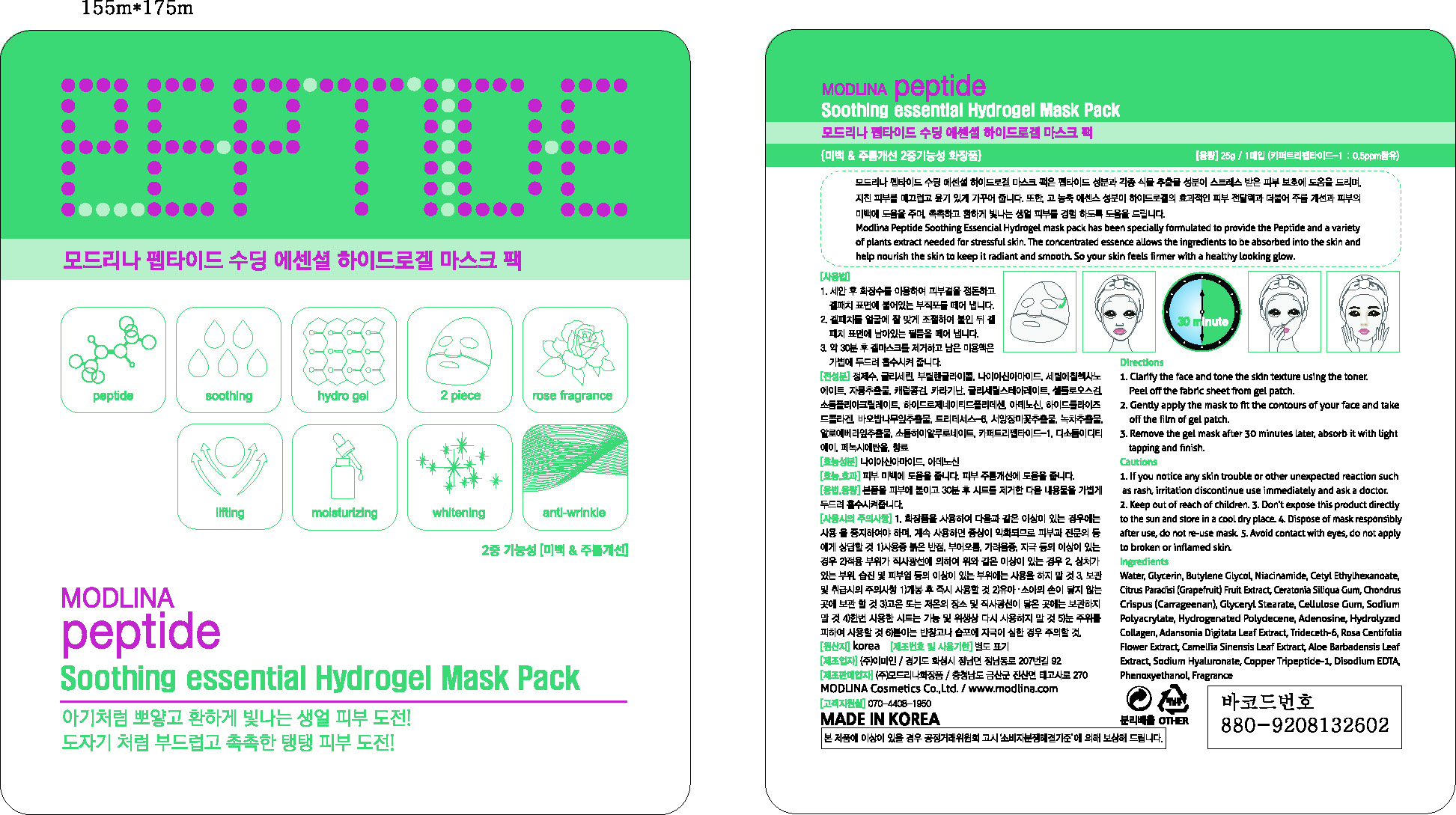 DRUG LABEL: MODLINA PEPTIDE SOOTHING ESSENTIAL HYDROGEL MASK PACK
NDC: 58895-1001 | Form: LIQUID
Manufacturer: Modlina Cosmetics Co., Ltd
Category: otc | Type: HUMAN OTC DRUG LABEL
Date: 20130812

ACTIVE INGREDIENTS: GLYCERIN 0.01 g/1 g
INACTIVE INGREDIENTS: WATER; HYALURONATE SODIUM; NIACINAMIDE; CETYL ETHYLHEXANOATE

Drug Facts

ACTIVE INGREDIENT

glycerin

INACTIVE INGREDIENT

water, butylene glycol, niacinamide, cetyl ethylhexanoate, grapefruit fruit ext, ceratonia siliqua gum, carrageenan, glyceryl stearate, cellulose gum, sodium polyacrylate, hydrogenated polydecene, adenosine, hydrolyzed gollagen, adansonia digitata leaf ext, trideceth-6, rosa centifolia flower ext, camellia sinensis leaf ext, aloe barbadensis leaf ext, sodium hyaluronate, copper tripeptide-1, disodium edta, phenoxyethanol, fragrance

PURPOSE

whitening, anti-wrinkle

keep out of reach of the children

INDICATIONS AND USAGE

clarify the face and tone the skin texture using the toner, peel off the fabric sheet from gel patch
gently apply the mask to fit the contours of your face and take off the film of gel patch
remove the gel mask hafter 30 minutes later, absorb it with tight tapping and finish

WARNINGS

if you notice any skin trouble or other unexpected reaction such as rash, irritation discontinue use immediately and ask a doctor
do not expose this product directly to the sun and store in a cool dry place

DOSAGE AND ADMINISTRATION

for external use only